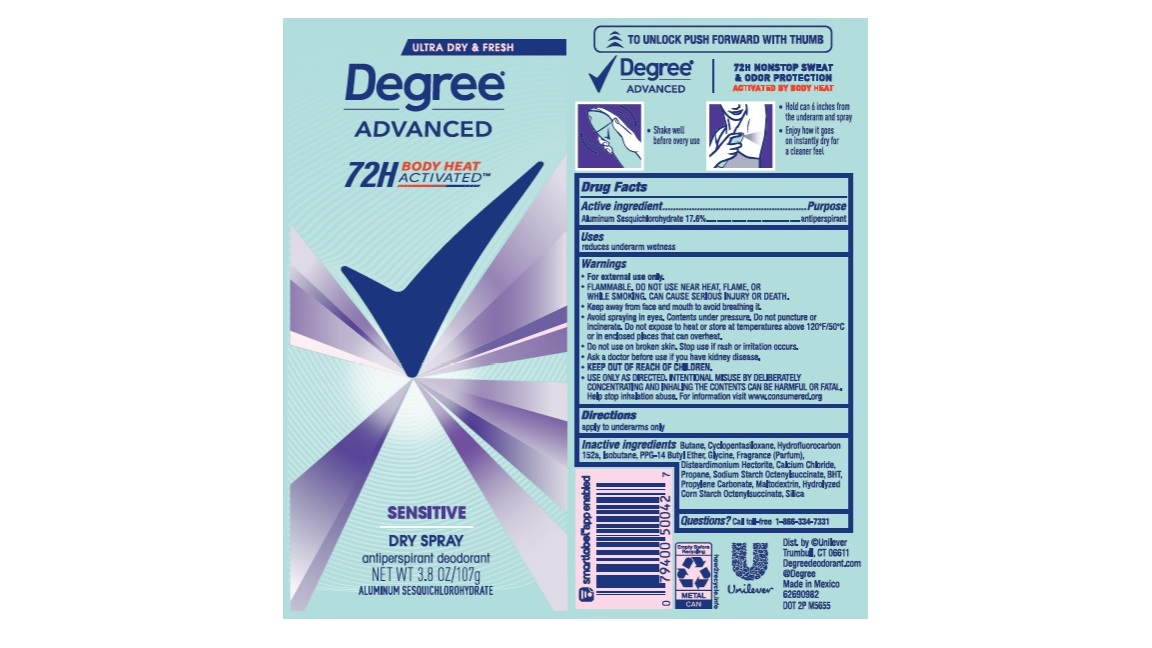 DRUG LABEL: Degree
NDC: 64942-2221 | Form: AEROSOL, SPRAY
Manufacturer: Conopco, Inc. d/b/a Unilever
Category: otc | Type: HUMAN OTC DRUG LABEL
Date: 20241106

ACTIVE INGREDIENTS: ALUMINUM SESQUICHLOROHYDRATE 17.6 g/100 g
INACTIVE INGREDIENTS: SILICON DIOXIDE; MALTODEXTRIN; PROPYLENE CARBONATE; GLYCINE; ISOBUTANE; BUTANE; 1,1-DIFLUOROETHANE; CYCLOMETHICONE 5; PPG-14 BUTYL ETHER; DISTEARDIMONIUM HECTORITE; CALCIUM CHLORIDE; PROPANE; BUTYLATED HYDROXYTOLUENE

Degree Advanced Sensitive Dry Spray 72H Antiperspirant Deodorant

Drug Facts

Active ingredient

Aluminum Sesquichlorohydrate (17.6%)

Purpose

antiperspirant

Uses

reduces underarm wetness

Directions

For underarms use only

Inactive ingredients

Butane, Cyclopentasiloxane, Hydrofluorocarbon 152a, Isobutane, PPG-14 Butyl Ether, Glycine, Fragrance (Parfum), Disteardimonium Hectorite, Calcium Chloride, Propane, Sodium Starch Octenylsuccinate, BHT, Propylene Carbonate, Maltodextrin, Hydrolyzed Corn Starch Octenylsuccinate, Silica

Questions?

Call toll-free 1-866-334-7331